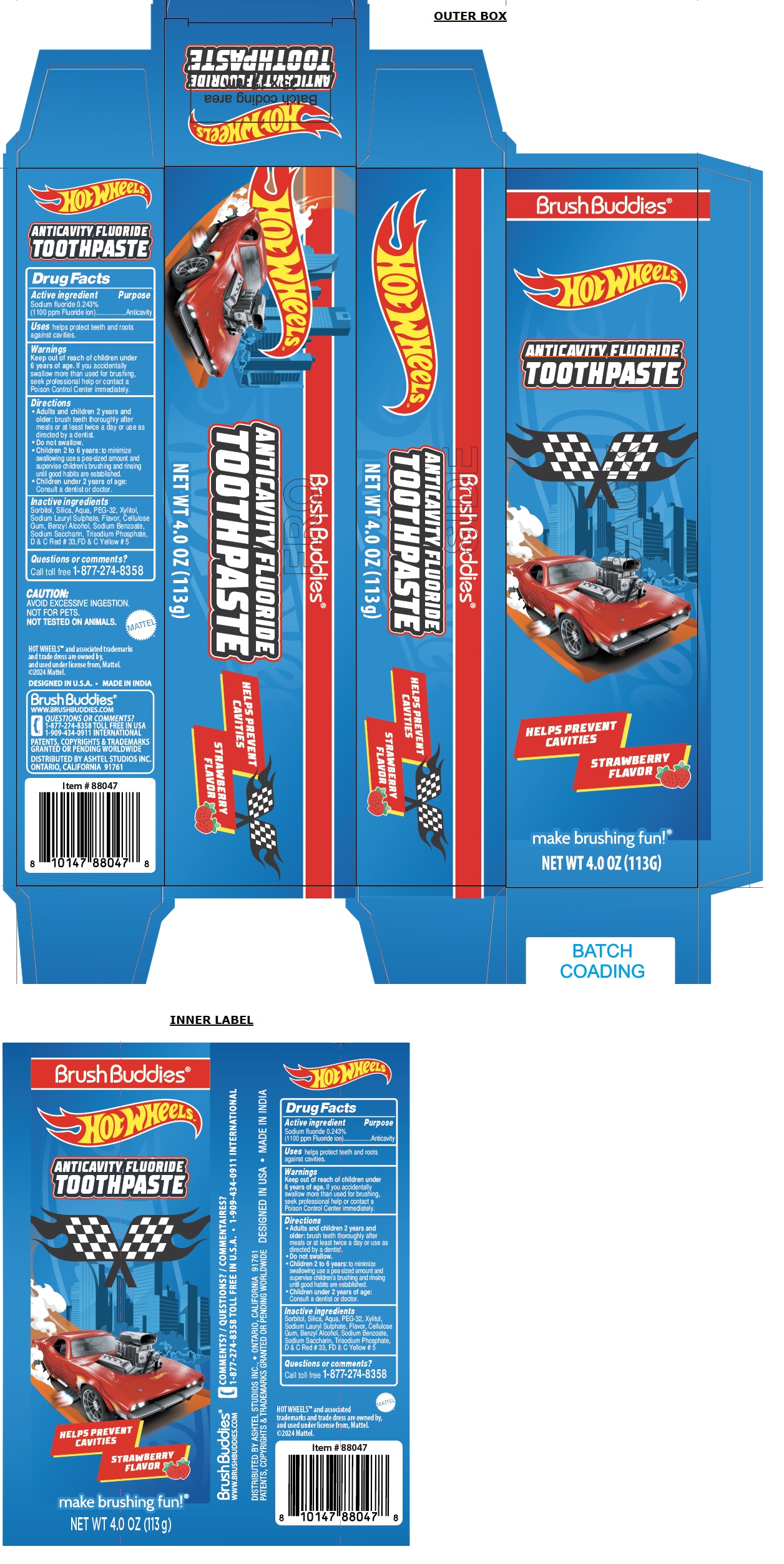 DRUG LABEL: Brush Buddies - Hot Wheels ANTICAVITY FLUORIDE
NDC: 70108-083 | Form: PASTE, DENTIFRICE
Manufacturer: Ashtel Studios Inc.
Category: otc | Type: HUMAN OTC DRUG LABEL
Date: 20240529

ACTIVE INGREDIENTS: SODIUM FLUORIDE 0.243 g/100 g
INACTIVE INGREDIENTS: SORBITOL; SILICON DIOXIDE; WATER; POLYETHYLENE GLYCOL 1600; XYLITOL; SODIUM LAURYL SULFATE; CARBOXYMETHYLCELLULOSE SODIUM, UNSPECIFIED; BENZYL ALCOHOL; SODIUM BENZOATE; SACCHARIN SODIUM; SODIUM PHOSPHATE, TRIBASIC, ANHYDROUS; D&C RED NO. 33; FD&C YELLOW NO. 5

Brush Buddies® Hot WHeeLsTM ANTICAVITY FLUORIDE TOOTHPASTE

Active ingredient

Sodium fluoride 0.243%
(1100 ppm Fluoride ion)

Purpose

Anticavity

Uses

helps protect teeth and roots against cavities.

Warnings

Keep out of reach of children under 6 years of age. If you accidentally swallow more than used for brushing, seek professional help or contact a Poison Control Center immediately.

Directions

• Adults and children 2 years and older: brush teeth thoroughly after meals or at least twice a day or use as directed by a dentist.
• Do not swallow.
• Children 2 to 6 years: to minimize swallowing use a pea-sized amount and supervise children's brushing and rinsing until good habits are established.
• Children under 2 years of age: Consult a dentist or doctor.

Inactive ingredients

Sorbitol, Silica, Aqua, PEG-32, Xylitol, Sodium Lauryl Sulfate, Flavor, Cellulose Gum, Benzyl Alcohol, Sodium Benzoate, Sodium Saccharin, Trisodium Phosphate, D & C Red # 33, FD & C Yellow # 5

Questions or comments?

Call toll free 1-877-274-8358

HELPS PREVENT CAVITIES

STRAWBERRY FLAVOR

make brushing fun!®

CAUTION:
AVOID EXCESSIVE INGESTION.
NOT FOR PETS.
NOT TESTED ON ANIMALS.

MATTEL
HOT WHEELS™ and associated trademarks and trade dress are owned by, and used under license from, Mattel.
©2024 Mattel.

DESIGNED IN U.S.A • MADE IN INDIA

Brush Buddies®
WWW.BRUSHBUDDIES.COM

1-909-434-0911 INTERNATIONAL

PATENTS, COPYRIGHTS & TRADEMARKS GRANTED OR PENDING WORLDWIDE

DISTRIBUTED BY ASHTEL STUDIOS INC.
ONTARIO, CALIFORNIA 91761